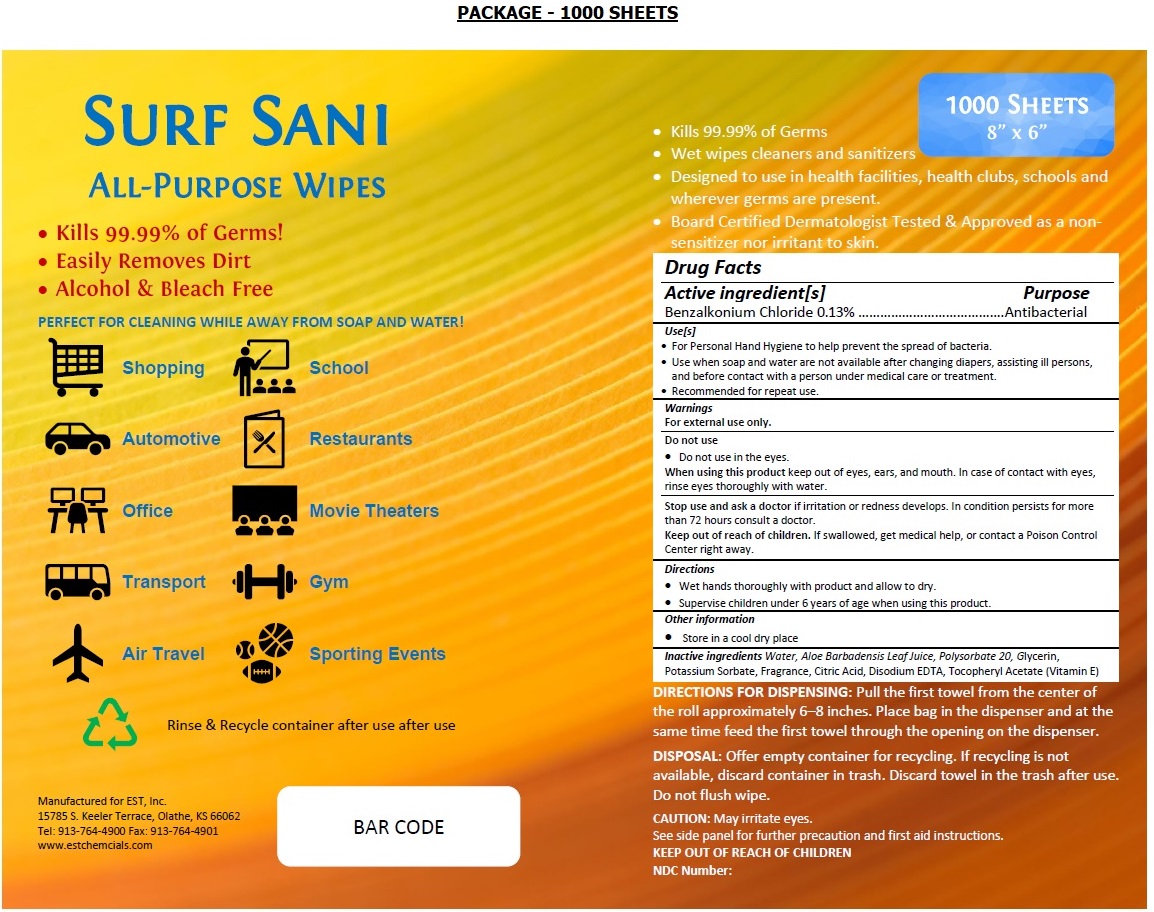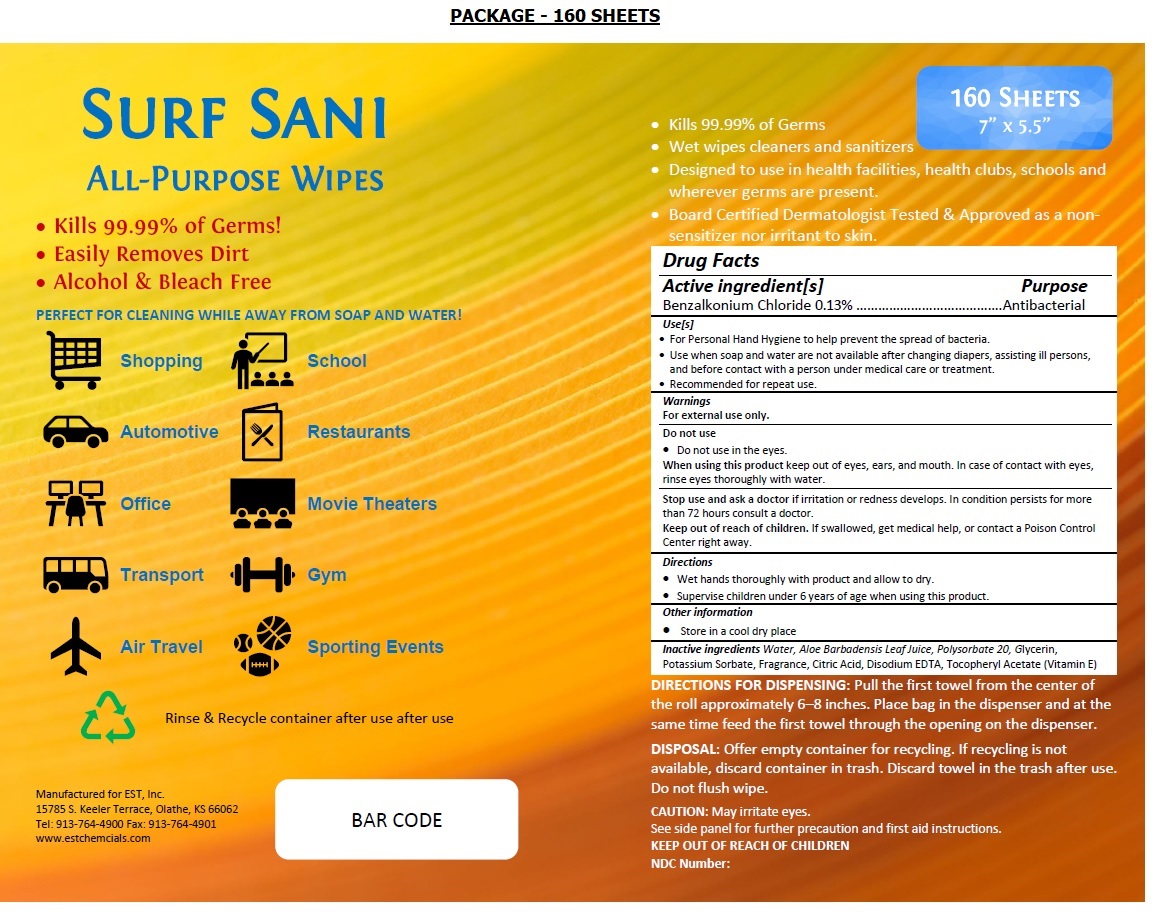 DRUG LABEL: SURF SANI ALL-PURPOSE WIPES
NDC: 77845-100 | Form: CLOTH
Manufacturer: Enviro Science Technology Inc
Category: otc | Type: HUMAN OTC DRUG LABEL
Date: 20201224

ACTIVE INGREDIENTS: BENZALKONIUM CHLORIDE 0.13 g/100 mL
INACTIVE INGREDIENTS: WATER; ALOE VERA LEAF; POLYSORBATE 20; GLYCERIN; POTASSIUM SORBATE; CITRIC ACID MONOHYDRATE; EDETATE DISODIUM ANHYDROUS; .ALPHA.-TOCOPHEROL ACETATE

SURF SANI ALL-PURPOSE WIPES

Active ingredient[s]

Benzalkonium Chloride 0.13%

Purpose

Antibacterial

Use[s]

- For Personal Hand Hygiene to help prevent the spread of bacteria.
- Use when soap and water are not available after changing diapers, assisting ill persons, and before contact with a person under medical care or treatment.
- Recommended for repeat use.

Warnings

For external use only.

Do not use
• Do not use in the eyes.

When using this product keep out of eyes, ears, and mouth. In case of contact with eyes, rinse eyes thoroughly with water.

Stop use and ask a doctor if irritation or redness develops. In condition persists for more than 72 hours consult a doctor.

Keep out of reach of children. If swallowed, get medical help, or contact a Poison Control Center right away.

Directions

• Wet hands thoroughly with product and allow to dry.
• Supervise children under 6 years of age when using this product.

Other information

• Store in a cool dry place

Inactive ingredients

Water, Aloe Barbadensis Leaf Juice, Polysorbate 20, Glycerin, Potassium Sorbate, Fragrance, Citric Acid, Disodium EDTA, Tocopheryl Acetate (Vitamin E)

• Kills 99.99% of Germs!
• Easily Removes Dirt
• Alcohol & Bleach Free

PERFECT FOR CLEANING WHILE AWAY FROM SOAP AND WATER!

Shopping School

Automotive Restaurants

Office Movie Theaters

Transport Gym

Air Travel Sporting Events

Manufactured for EST, Inc.
15785 S. Keeler Terrace, Olathe, KS 66062
Tel: 913-764-4900 Fax: 913-764-4901
www.estchemcials.com

• Kills 99.99% of Germs
• Wet wipes cleaners and sanitizers
• Designed to use in health facilities, health clubs, schools and wherever germs are present.
• Board Certified Dermatologist Tested & Approved as a non-sensitizer nor irritant to skin.

DIRECTIONS FOR DISPENSING: Pull the first towel from the center of the roll approximately 6–8 inches. Place bag in the dispenser and at the
same time feed the first towel through the opening on the dispenser.

DISPOSAL: Offer empty container for recycling. If recycling is not available, discard container in trash. Discard towel in the trash after use.
Do not flush wipe.

CAUTION: May irritate eyes.
See side panel for further precaution and first aid instructions.

KEEP OUT OF REACH OF CHILDREN